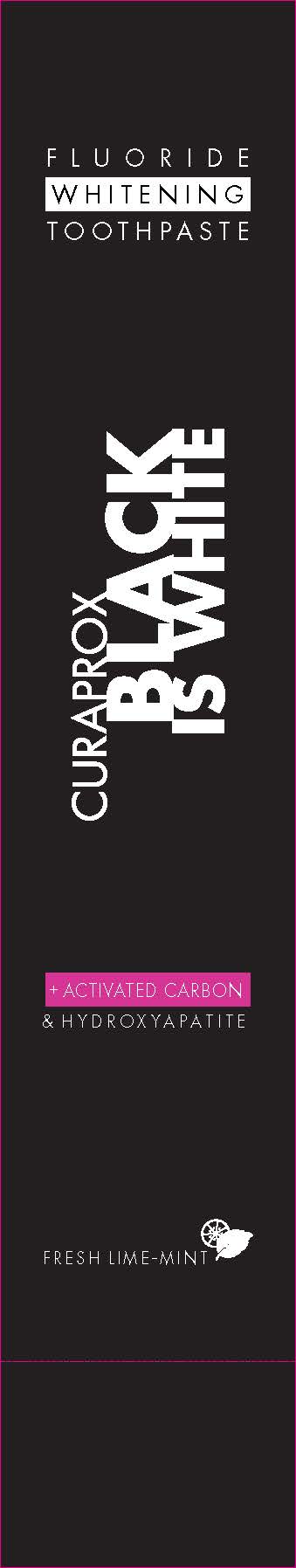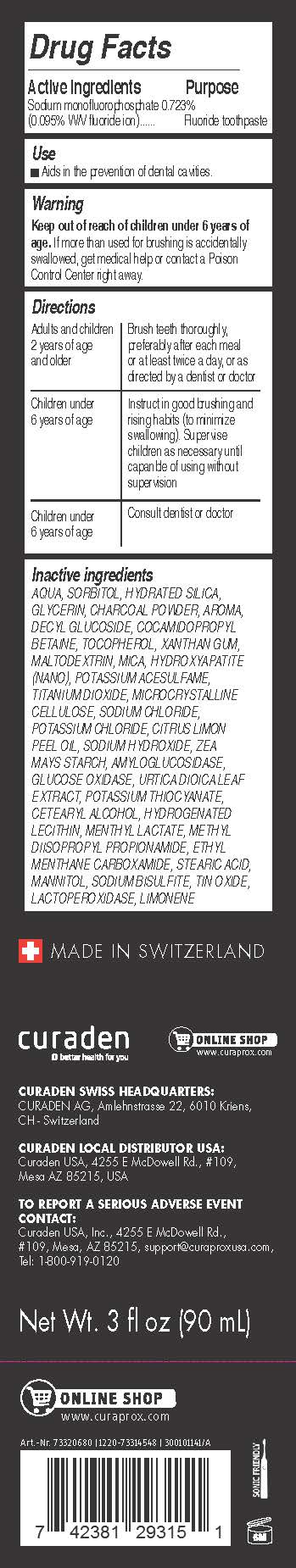 DRUG LABEL: Curaprox Black Is White
NDC: 71112-001 | Form: PASTE, DENTIFRICE
Manufacturer: Curaden AG
Category: otc | Type: HUMAN OTC DRUG LABEL
Date: 20220712

ACTIVE INGREDIENTS: SODIUM MONOFLUOROPHOSPHATE 0.095 g/100 mL
INACTIVE INGREDIENTS: POTASSIUM THIOCYANATE

Keep out of reach of children under 6 years of age. If more than used for brushing is accidentally swallowed, get medical help or contact a Poison Control Center right away.

DOSAGE FORMS AND STRENGTHS

Adults and children 2 years of age and older:
Brush teeth thoroughly, preferably after each meal or at least twice a day, or as directed by a dentist or doctor.

Children under 6 years of age:
Instruct in good brushing and rising habits (to minimize swallowing). Supervise children as necessary until capanble of using without supervision.

Consult dentist or doctor.

HEALTH CLAIM

Aids in the prevention of dental cavities.

INACTIVE INGREDIENT

AQUA, SORBITOL, HYDRATED SILICA, GLYCERIN, CHARCOAL POWDER, AROMA, DECYL GLUCOSIDE, COCAMIDOPROPYL BETAINE, TOCOPHEROL, XANTHAN GUM, MALTODEXTRIN, MICA, HYDROXYAPATITE (NANO), POTASSIUM ACESULFAME, TITANIUM DIOXIDE, MICROCRYSTALLINE CELLULOSE, SODIUM CHLORIDE, POTASSIUM CHLORIDE, CITRUS LIMON PEEL
OIL, SODIUM HYDROXIDE, ZEA MAYS STARCH, AMYLOGLUCOSIDASE, GLUCOSE OXIDASE, URTICA DIOICA LEAF EXTRACT, POTASSIUM THIOCYANATE, CETEARYL ALCOHOL, HYDROGENATED LECITHIN, MENTHYL LACTATE, METHYL DIISOPROPYL PROPIONAMIDE, ETHYL MENTHANE CARBOXAMIDE, STEARIC ACID, MANNITOL, SODIUM BISULFITE, TIN OXIDE, LACTOPEROXIDASE, LIMON

ACTIVE INGREDIENT

Sodium monofluorophosphate 0.723%
(0.095% W/V fluoride ion)

Fluoride toothpaste

ASK DOCTOR

Children under 6 years of age:
Consult dentist or doctor

Keep out of reach of children under 6 years of age.

OVERDOSAGE

If more than used for brushing is accidentally swallowed, get medical help or contact a Poison Control Center right away.

ROUTE, METHOD AND FREQUENCY OF ADMINISTRATION

Brush teeth thoroughly, preferably after each meal or at least twice a day, or as directed by a dentist or doctor.

Keep out of reach of children under 6 years of age. If more than used for brushing is accidentally swallowed, get medical help or contact a Poison Control Center right away.

DOSAGE AND ADMINISTRATION

Apply small bead on bristles of toothbrush. Use bristles with toothpaste to brush all around teeth to include gum line.

Use

Aid in the prevention of dental cavities.

Use

Aids in the prevention of cavities.